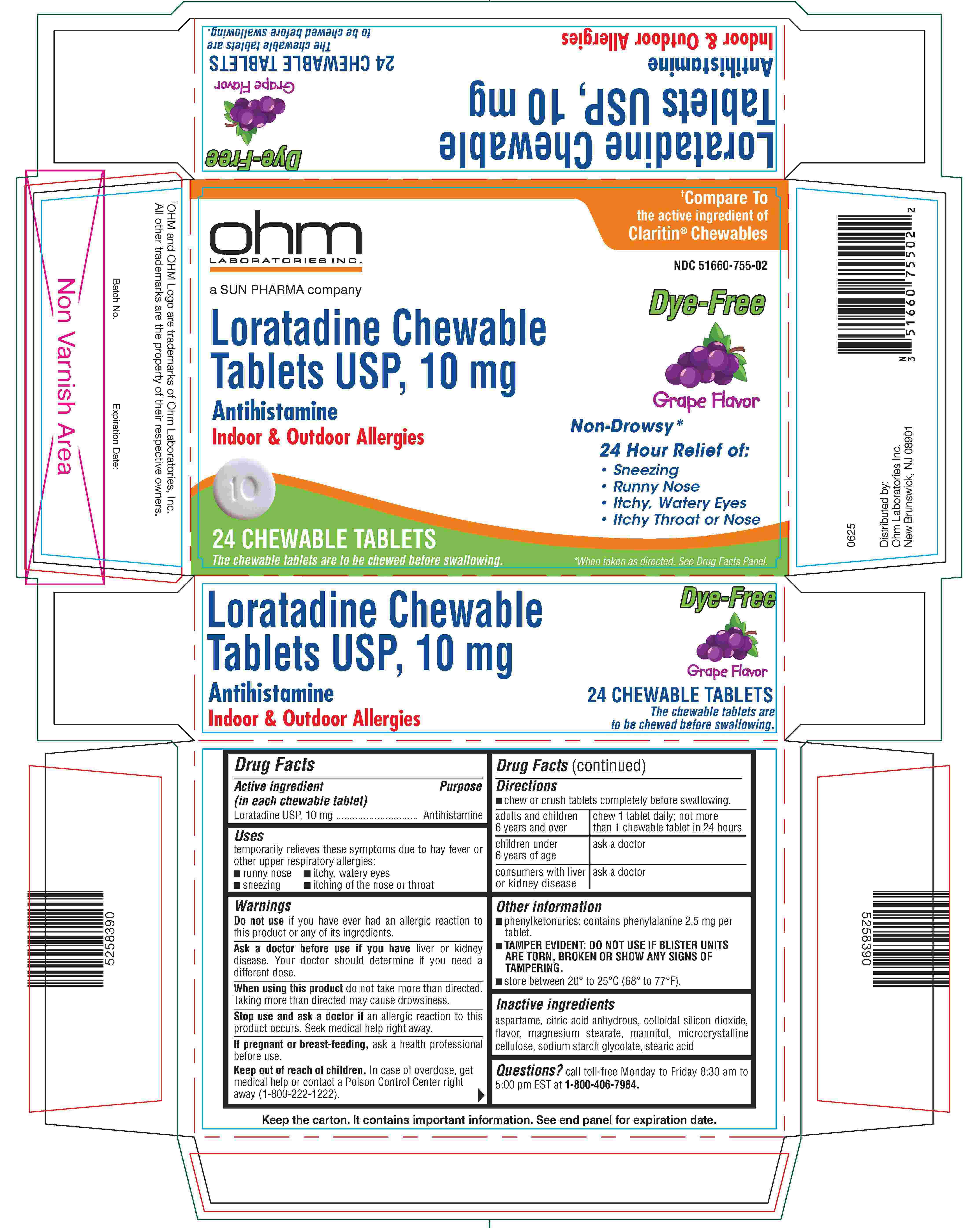 DRUG LABEL: DYE-FREE LORATADINE
NDC: 51660-755 | Form: TABLET, CHEWABLE
Manufacturer: Ohm Laboratories Inc.
Category: otc | Type: HUMAN OTC DRUG LABEL
Date: 20260115

ACTIVE INGREDIENTS: LORATADINE 5 mg/1 1
INACTIVE INGREDIENTS: ASPARTAME; ANHYDROUS CITRIC ACID; SILICON DIOXIDE; MAGNESIUM STEARATE; MANNITOL; MICROCRYSTALLINE CELLULOSE; SODIUM STARCH GLYCOLATE TYPE A POTATO; STEARIC ACID

Dye-Free Loratadine Chewable Tablets USP, 10 mg

Drug Facts

Active ingredient (in each chewable tablet)

Loratadine USP, 10 mg

Purpose

Antihistamine

Uses

temporarily relieves these symptoms due to hay fever or other upper respiratory allergies:

- runny nose
- sneezing
- itchy, watery eyes
- itching of the nose or throat

Warnings

Do not use if you have ever had an allergic reaction to this product or any of its ingredients.

Ask a doctor before use if you have liver or kidney disease. Your doctor should determine if you need a different dose.

When using this product do not take more than directed. Taking more than directed may cause drowsiness.

Stop use and ask a doctor if an allergic reaction to this product occurs. Seek medical help right away.

PREGNANCY OR BREAST FEEDING

If pregnant or breast-feeding, ask a health professional before use.

Keep out of reach of children. In case of overdose, get medical help or contact a Poison Control Center right away (1-800-222-1222).

Directions

- chew or crush tablets completely before swallowing.

adults and children 6 years and over | chew 1 tablets daily; not more than 1 chewable tablets in 24 hours
children under 6 years of age | ask a doctor
consumers with liver or kidney disease | ask a doctor

Other information

- phenylketonurics: contains phenylalanine 1.25 mg per tablet.
- TAMPER EVIDENT: DO NOT USE IF BLISTER UNITS ARE TORN, BROKEN OR SHOW ANY SIGNS OF TAMPERING.
- store between 20° to 25°C (68° to 77°F).

Inactive ingredients

aspartame, citric acid anhydrous, colloidal silicon dioxide, flavor, magnesium stearate, mannitol, microcrystalline cellulose, sodium starch glycolate, stearic acid

Questions?

call toll-free Monday to Friday 8:30 am to 5:00 pm EST at 1-800-406-7984.

Keep the carton. It contains important information. See end panel for expiration date.

Distributed by:
Ohm Laboratories Inc.
New Brunswick, NJ 08901

0625